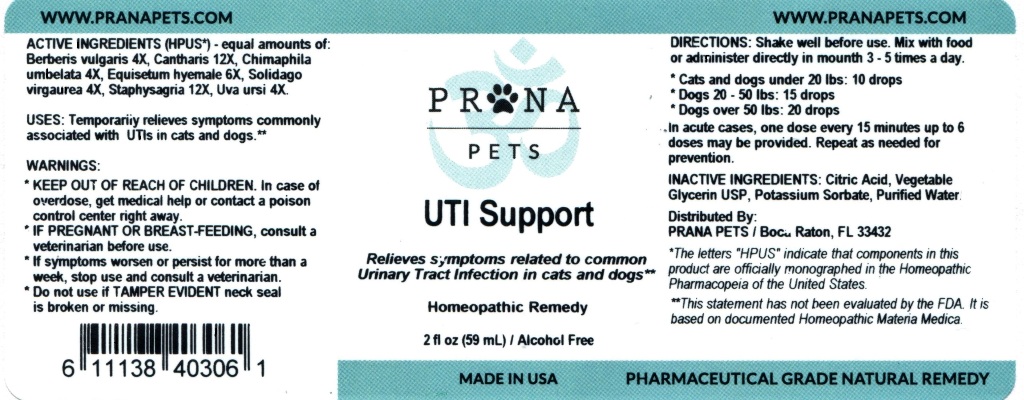 DRUG LABEL: UTI Support
NDC: 86066-001 | Form: LIQUID
Manufacturer: Surefreight Global LLC, DBA PRANAPETS
Category: homeopathic | Type: OTC ANIMAL DRUG LABEL
Date: 20200217

ACTIVE INGREDIENTS: BERBERIS VULGARIS ROOT BARK 4 [hp_X]/59 mL; LYTTA VESICATORIA 12 [hp_X]/59 mL; CHIMAPHILA UMBELLATA 4 [hp_X]/59 mL; EQUISETUM HYEMALE 6 [hp_X]/59 mL; SOLIDAGO VIRGAUREA FLOWERING TOP 4 [hp_X]/59 mL; DELPHINIUM STAPHISAGRIA SEED 12 [hp_X]/59 mL; ARCTOSTAPHYLOS UVA-URSI LEAF 4 [hp_X]/59 mL
INACTIVE INGREDIENTS: WATER; GLYCERIN; CITRIC ACID MONOHYDRATE; POTASSIUM SORBATE

UTI Support

ACTIVE INGREDIENT

ACTIVE INGREDIENTS (HPUS*) - equal amounts of: Berberis vulgaris 4X, Cantharis 12X, Chimaphila umbelata 4X, Equisetum hyemale 6X, Solidago virgaurea 4X, Staphysagria 12X, Uva ursi 4X.

* The letters "HPUS" indicate that components in this product are officially monographed in the Homeopathic Pharmacopeia of the United States.

INDICATIONS AND USAGE

USES: Temporarily relieves symptoms commonly associated with UTIs in cats and dogs.**

** This statement has not been evaluated by the FDA. It is based on documented Homeopathic Materia Medica.

WARNINGS:

- KEEP OUT OF REACH OF CHILDREN. In case of overdose, get medical help or contact a poison control center right away.
- IF PREGNANT OR BREAST-FEEDING, consult a veterinarian before use.
- If symptoms worsen or persist for more than a week, stop use and consult a veterinarian.
- Do not use if TAMPER EVIDENT neck seal is broken or missing.

DOSAGE AND ADMINISTRATION

DIRECTIONS: Shake well before use.Mix with food or administer directly in mouth 3 - 5 times a day.

- Cats and dogs under 20 lbs: 10 drops
- Dogs 20 - 50 lbs: 15 drops
- Dogs over 50 lbs: 20 drops

In acute cases, one dose every 15 minutes up to 6 doses may be provided. Repeat as needed for prevention.

INACTIVE INGREDIENT

INACTIVE INGREDIENTS: Citric Acid, Vegetable Glycerin USP, Potassium Sorbate, Purified Water.

QUESTIONS

Distributed by:

PRANA PETS / Boca Raton, FL 33432

www.pranapets.com

PACKAGE LABEL

PRANA PETS

UTI Support

Relieves symptoms related to common Urinary Tract Infecion in cats and dogs

Homeopathic Remedy

2 fl oz (59 mL) / Alcohol Free

Made in USA

Pharmaceutical Grade Natural Remedy